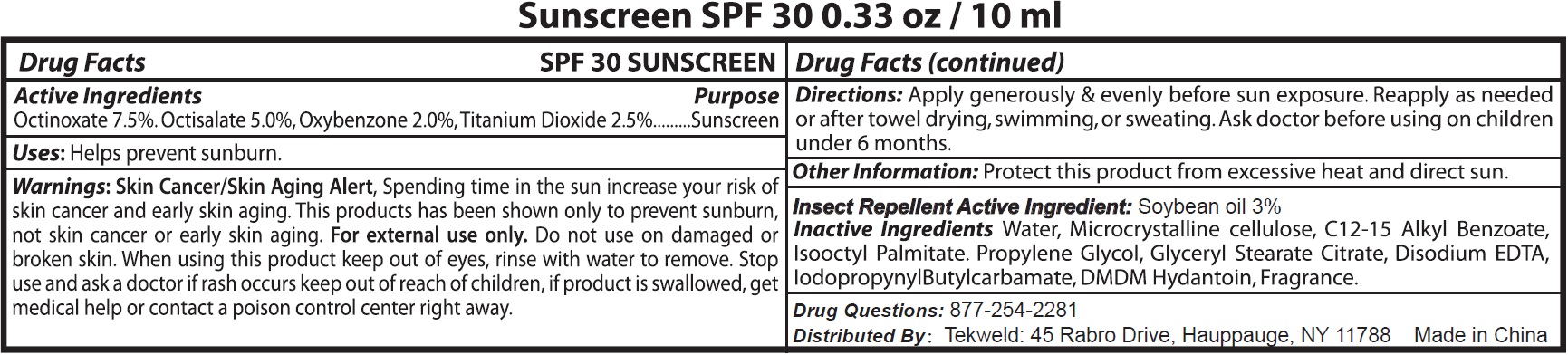 DRUG LABEL: SPF 30 Sunscreen with Soybean
NDC: 71160-010 | Form: SPRAY, SUSPENSION
Manufacturer: Tekweld Solutions, Inc.
Category: otc | Type: HUMAN OTC DRUG LABEL
Date: 20191226

ACTIVE INGREDIENTS: OCTINOXATE 75 mg/1 mL; OCTISALATE 50 mg/1 mL; OXYBENZONE 20 mg/1 mL; TITANIUM DIOXIDE 25 mg/1 mL
INACTIVE INGREDIENTS: WATER; MICROCRYSTALLINE CELLULOSE; ALKYL (C12-15) BENZOATE; ISOCETYL PALMITATE; PROPYLENE GLYCOL; GLYCERYL STEARATE CITRATE; EDETATE DISODIUM ANHYDROUS; IODOPROPYNYL BUTYLCARBAMATE; DMDM HYDANTOIN

SPF 30 Sunscreen Spray with Soybean Oil

Active Ingredients

Octinoxate 7.5%,

Octisalate 5.0%,

Oxybenzone 2.0%

Titanium Dioxide 2.5%

Soybean oil 3%

Purpose

Sunscreen

Uses

• Helps prevent sunburn

WARNINGS:

Skin Cancer/Skin Aging Alert: Spending time in the sun increase your risk of skin cancer and early skin aging.
This products has been shown only to prevent sunburn, not skin cancer or early skin aging.

For external use only.

Do not use

on damaged or broken skin.

When using this product

keep out of eyes. Rinse with water to remove.

Stop use and ask a doctor

if rash occurs.

Keep out of reach of children.

If product swallowed, get medical help or contact a Poison Control Center right away.

Directions

Apply generously & evenly before sun exposure.Reapply as needed or after towel drying, swimming, or sweating. Ask doctor before using on children under 6 months.

Other information

Protect this product from excessive heat and direct sun

Insect Repellent Active Ingredient: Soybean oil 3% Inactive ingredients

Water, Microcrystalline cellulose, C12-15 Alkyl Benzoate, Isooctyl Palmitate, Propylene Glycol, Glyceryl Stearate Citrate, Disodium EDTA, Iodopropynyl Butylcarbamate, DMDM Hydantoin, Fragrance.

Drug Questions:

877-254-2281

Distributed By:

Tekweld: 45 Rabro Drive, Hauppauge, NY11788